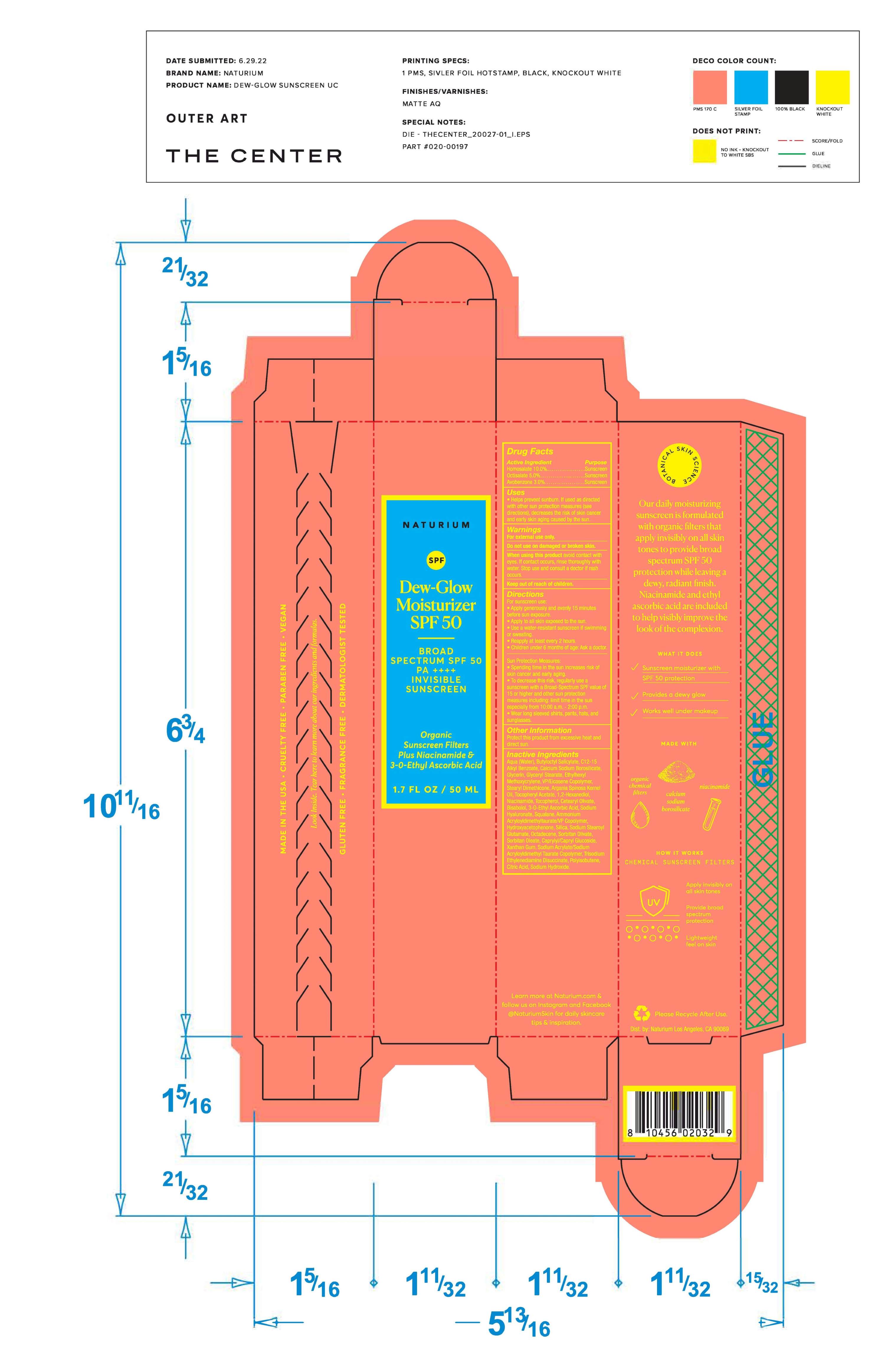 DRUG LABEL: NATURIUM Dew-Glow Moisturizer SPF 50
NDC: 59735-338 | Form: CREAM
Manufacturer: MANA Products, Inc
Category: otc | Type: HUMAN OTC DRUG LABEL
Date: 20240822

ACTIVE INGREDIENTS: OCTISALATE 5 g/1 mL; AVOBENZONE 3 g/1 mL; HOMOSALATE 10 g/1 mL
INACTIVE INGREDIENTS: EICOSYL POVIDONE; STEARYL DIMETHICONE (400 MPA.S AT 50C); CETEARYL OLIVATE; AMMONIUM ACRYLOYLDIMETHYLTAURATE/VP COPOLYMER; SILICON DIOXIDE; POLYISOBUTYLENE (65000 MW); CAPRYLYL/CAPRYL OLIGOGLUCOSIDE; BUTYLOCTYL SALICYLATE; .ALPHA.-BISABOLOL, (+)-; TRISODIUM ETHYLENEDIAMINE DISUCCINATE; SORBITAN OLIVATE; ARGAN OIL; .ALPHA.-TOCOPHEROL, DL-; SQUALANE; ANHYDROUS CITRIC ACID; .ALPHA.-TOCOPHEROL ACETATE, D-; HYDROXYETHYL ACRYLATE/SODIUM ACRYLOYLDIMETHYL TAURATE COPOLYMER (45000 MPA.S AT 1%); SODIUM HYDROXIDE; ETHYLHEXYL METHOXYCRYLENE; HYDROXYACETOPHENONE; SODIUM STEAROYL GLUTAMATE; OCTADECENE; XANTHAN GUM; 1,2-HEXANEDIOL; 3-O-ETHYL ASCORBIC ACID; HYALURONATE SODIUM; NIACINAMIDE; SORBITAN MONOOLEATE; WATER; ALKYL (C12-15) BENZOATE; CALCIUM ALUMINUM BOROSILICATE; GLYCERIN; GLYCERYL STEARATE SE

NATURIUM Dew-Glow Moisturizer SPF 50

Active Ingredients

Avobenzone 3%

Homosalate 10%

Octisalate 5%

Purpose

Sunscreen

Uses

Helps prevent sunburn. If used as directed with other sun protection measures (see directions), decreases the risk of skin cancer and early skin aging caused by the sun.

Warnings

For external use only. Do not use on damaged or broken skin. Stop use and ask doctor if rash occurs.

Warnings-When using

When using this product keep out of eyes. Rinse with water to remove.

Keep out of reach of children. If swallowed, get medical help, or contact a Poison Control Center right away.

Directions

Apply liberally 15 minutes before sun exposure. Use a water-resistant sunscreen if swimming or sweating. Reapply at least every 2 hours, Children under 6 months: ask a doctor.
Sun Protection Measures: Spending time in the sun increases risk of skin cancer and early aging. To decrease
this risk, regularly use a sunscreen with a Broad-Spectrum SPF value of 15 or higher and other sun protection measures including: limit time in the sun especially from 10:00 a.m. - 2:00 p.m. Wear long sleeved shirts, pants, hats, and sunglasses.

Inactive Ingredients

Aqua/Water/Eau, Butyloctyl Salicylate, C12-15 Alkyl Benzoate, Calcium Sodium Borosilicate, Glycerin, Glyceryl Stearate, Ethylhexyl Methoxycrylene, VP/Eicosene Copolymer, Stearyl Dimethicone, Argania Spinosa Kernel Oil, Tocopheryl Acetate, 1,2-Hexanediol, Niacinamide, Tocopherol, Cetearyl Olivate, Ammonium Acryloyldimethyltaurate/VP Copolymer, Hydroxyacetophenone, Silica, Sodium Stearoyl Glutamate, Octadecene, Sorbitan Olivate, Xanthan Gum, Bisabolol, 3-o-ethyl ascorbic acid, Sodium Hyaluronate, Squalane, Sodium Acrylate/Sodium Acryloyldimethyl Taurate Copolymer, Trisodium Ethylenediamine Disuccinate, Polyisobutene, Citric Acid, Sodium Hydroxide, Sorbitan Oleate, Caprylyl/Capryl Glucoside.

Other Information

Protect this product from excessive heat and direct sun.

RECENT MAJOR CHANGES

DOSAGE & ADMINISTRATION